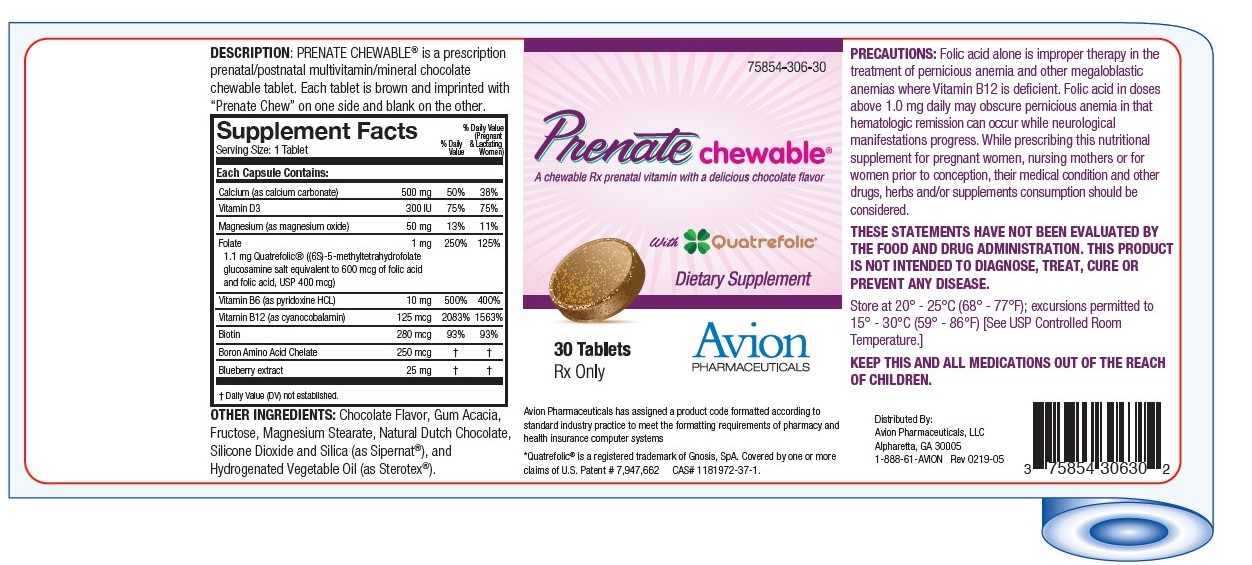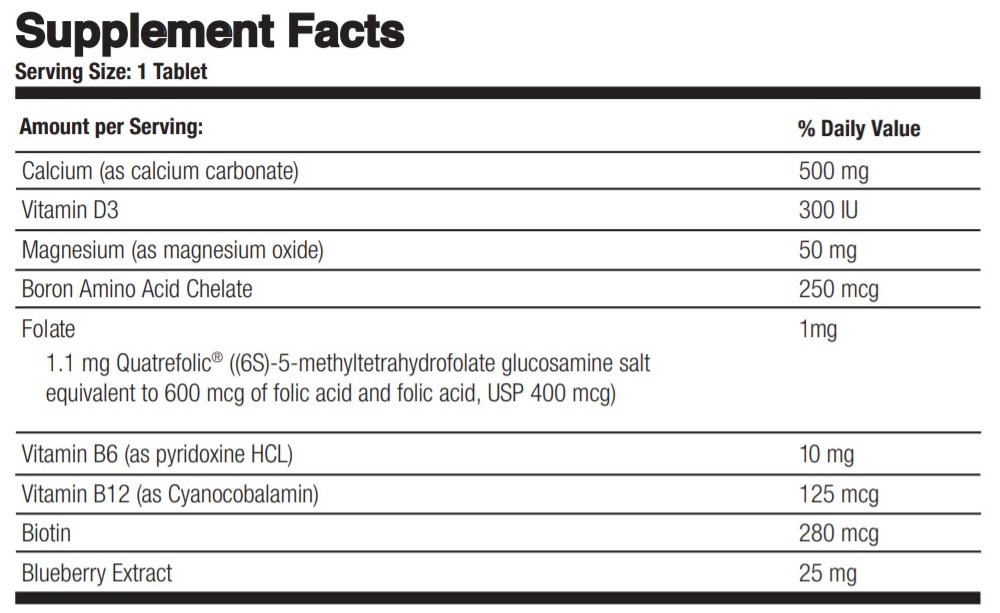 DRUG LABEL: Prenate Chewable
NDC: 75854-306 | Form: TABLET, CHEWABLE
Manufacturer: Avion Pharmaceuticals, LLC
Category: prescription | Type: HUMAN PRESCRIPTION DRUG LABEL
Date: 20240119

ACTIVE INGREDIENTS: CALCIUM CARBONATE 500 mg/1 1; CHOLECALCIFEROL 300 [iU]/1 1; MAGNESIUM OXIDE 50 mg/1 1; BORON 250 ug/1 1; FOLIC ACID 1 mg/1 1; PYRIDOXINE HYDROCHLORIDE 10 mg/1 1; CYANOCOBALAMIN 125 mg/1 1; BIOTIN 280 ug/1 1; BILBERRY 25 mg/1 1
INACTIVE INGREDIENTS: FRUCTOSE; ACACIA; MAGNESIUM STEARATE; SILICON DIOXIDE

Prenate chewable®

A chewable Rx prenatal vitamin with a delicious chocolate flavor

Rx Only

DESCRIPTION

DESCRIPTION: PRENATE CHEWABLE® is a prescription prenatal/postnatal multivitamin/mineral chocolate chewable tablet. Each tablet is brown and imprinted with "Prenate Chew" on one side and blank on the other.

INACTIVE INGREDIENT

OTHER INGREDIENTS: Chocolate Flavor, Gum Acacia, Fructose, Magnesium Stearate, Natural Dutch Chocolate, Silicone Dioxide and Silica (as Sipernat®), and Hydrogenated Vegetable Oil (as Sterotex®).

INDICATIONS AND USAGE

INDICATIONS: PRENATE CHEWABLE® is a multivitamin/multimineral dietary supplement indicated for use in improving the nutritional status of women throughout pregnancy and in the postnatal period for both lactating and nonlactating mothers. PRENATE CHEWABLE™ can also be beneficial in improving the nutritional status of women prior to conception.

CONTRAINDICATIONS

CONTRAINDICATIONS: This product is contraindicated in patients with a known hypersensitivity to any of the ingredients.

KEEP THIS AND ALL MEDICATIONS OUT OF THE REACH OF CHILDREN.

PRECAUTIONS

PRECAUTIONS: Folic acid alone is improper therapy in the treatment of pernicious anemia and other megaloblastic anemias where Vitamin B12 is deficient. Folic acid in doses above 0.1 mg daily may obscure pernicious anemia in that hematologic remission can occur while neurological manifestations progress.

ADVERSE REACTIONS

ADVERSE REACTIONS: Allergic sensitization has been reported following both oral and parenteral administration of folic acid.

DOSAGE AND ADMINISTRATION: One tablet daily or as directed by a physician.

HOW SUPPLIED

HOW SUPPLIED: PRENATE CHEWABLE® is supplied in child-resistant bottles of 30 tablets (75854-306-30).

The listed product number is not a National Drug Code, but has instead merely been formatted to comply with standard industry practice for pharmacy and insurance computer systems.

STORAGE AND HANDLING

Store at 20° - 25°C (68° - 77°F); excursions permitted to 15° - 30°C (59° - 86°F) [See USP Controlled Room Temperature.]

THESE STATEMENTS HAVE NOT BEEN EVALUATED BY THE FOOD AND DRUG ADMINISTRATION. THIS PRODUCT IS NOT INTENDED TO DIAGNOSE, TREAT, CURE OR PREVENT ANY DISEASE.

MANUFACTURED FOR: Avion Pharmaceuticals, LLC
Atlanta, GA 30350
1-888-61-AVION

*Quatrefolic® is a registered trademark of Gnosis, SpA.Covered by one or more claims of U.S. Patent # 7,947,662 CAS# 1181972-37-1

Rev. 0619-05

PACKAGE LABEL

75854-306-30

Prenate chewable®

A chewable Rx prenatal vitamin with a delicious chocolate flavor

with Quatrefolic®

Dietary Supplement

30 Tablets

Rx Only

Avion
PHARMACEUTICALS